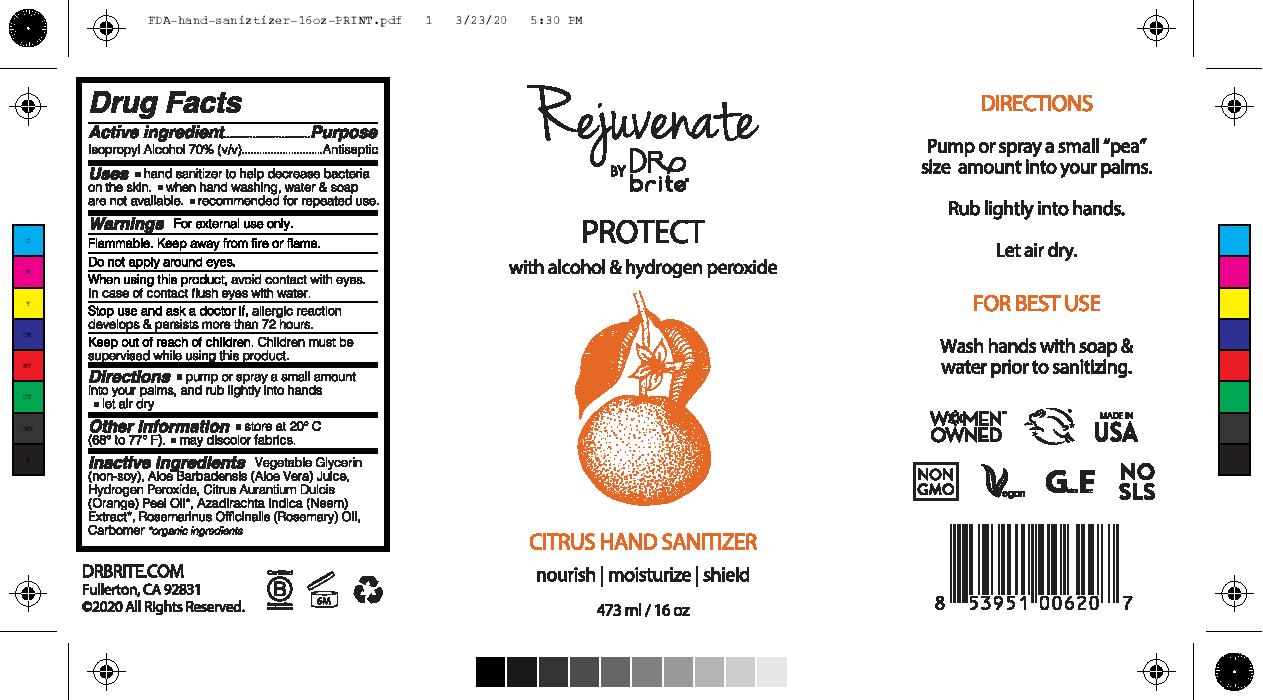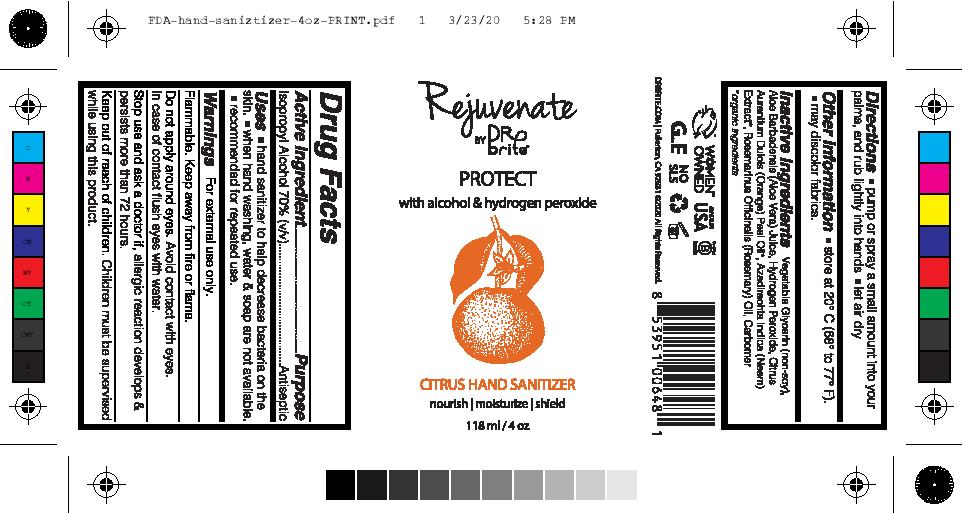 DRUG LABEL: Protect Hand Sanitizer
NDC: 74110-001 | Form: GEL
Manufacturer: Dr. Brite
Category: otc | Type: HUMAN OTC DRUG LABEL
Date: 20220106

ACTIVE INGREDIENTS: ISOPROPYL ALCOHOL 70 mL/100 mL
INACTIVE INGREDIENTS: AZADIRACHTA INDICA FLOWER; ROSEMARY OIL; CARBOMER COPOLYMER TYPE A; XANTHAN GUM; LEMON OIL; GRAPEFRUIT OIL; GLYCERIN; HYDROGEN PEROXIDE; WATER; ORANGE OIL

Active Ingredient(s)

Isopropyl Alcohol 70% v/v.

Purpose

Antiseptic

Use

- Hand Sanitizer to help reduce bacteria that potentially can cause disease.
- When hand wahing, water & soap are not available
- recommended for repeated use.

Warnings

For external use only. Flammable. Keep away from heat or flame. Do not apply around eyes.

Do not use

- in children less than 2 months of age
- on open skin wounds

When using this product keep out of eyes, ears, and mouth. In case of contact with eyes, rinse eyes thoroughly with water.

Stop use and ask a doctor if irritation or rash occurs. These may be signs of a serious condition.

Keep out of reach of children. If swallowed, get medical help or contact a Poison Control Center right away.

Directions

- pump or spray a small amount into your palms, and rub lightly into hands
- let air dry

Other information

- store at 20C (68 to 77F)
- may discolor fabrics

Inactive ingredients

vegtable glycerin, aloe barbadensis (alow vera) juice, hydrogen peroxide, citrus aurantium dulcis (orange) peel oil, azadirachta indica (neem) extract, rosemarinus officinalis (rosemary) oil, carbomer